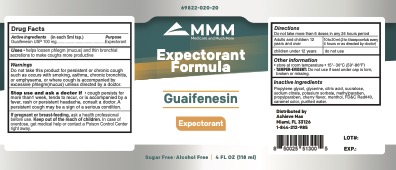 DRUG LABEL: MMM guaifenesin solution
NDC: 69822-020 | Form: SOLUTION
Manufacturer: Southern Sales & Services, Inc.
Category: otc | Type: HUMAN OTC DRUG LABEL
Date: 20211113

ACTIVE INGREDIENTS: GUAIFENESIN 100 mg/5 mL
INACTIVE INGREDIENTS: FD&C RED NO. 40; PROPYLENE GLYCOL; CITRIC ACID MONOHYDRATE; SUCRALOSE; WATER; POTASSIUM SORBATE; SODIUM CITRATE; MENTHOL; GLYCERIN

MMM - Guaifenesin Oral Solution

ACTIVE INGREDIENT

Each 5 mL (1 tespoonful) contains:

Guaifenesin USP 100mg

PURPOSE

Expectorant
SUGAR FREE / ALCOHOL

DO NOT USE

Do not take this product for persistent or chronic cough such as occurs with smoking, asthma, chronic bronchitis, or emphysema, or where cough is accompanied by excessive phlegm(mucus) unless directed by a doctor.

WARNINGS

Do not take this product for persistent or chronic cough such as occurs with smoking, asthma, chronic bronchitis, or emphysema, or where cough is accompanied by excessive phlegm(mucus) unless directed by a doctor.

Stop use and ask a doctor if

cough persists for more than1 week, tends to recur, or is accompanied by a fever, rash or persistent headache, consult a doctor. A persistent cough may be a sign of a serious condition.

If pregnant or breast-feeding, ask a health professional before use.

Keep out of reach of children. In case of overdose, get medical help or contact a Poison Control

Center right away.

INDICATIONS AND USAGE

Helps loosen phlegm (mucus) and thin bronchial secretions to make coughs more productive.

Stop use and ask a doctor if cough persists for more than 1 week, tends to recur, or is accompanied by fever, rash or persistent headache, consult a doctor. A persistent cough may be a sign of a serious condition.

DOSAGE AND ADMINISTRATION

Do not take more than 6 doses in any 24 hours period

Adults and children 12 years and over - 10 to 20ml (2 to 4 teaspoonfuls every 4 hours or as directed by doctor)

children under 12 years - do not use

STORAGE AND HANDLING

Store at room temperature 15º-30ºC (59º-86ºF)

Tamper-Evident: Do not use if seal under cap is torn, broken or missing.

INACTIVE INGREDIENT

Propylene glycol, glycerine, citric acid, sucralose, sodium citrate, potasium sorbate, methylparaben, propylparaben, cherry flavor, menthol, FD &C Red # 40 ,caramel color,purified water.

Keep out of reach of children. In case of overdose, get medical help or contact a Poison Control

Center right away.